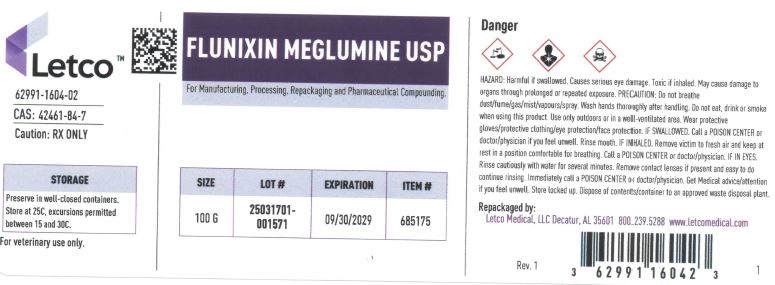 DRUG LABEL: Flunixin Meglumine
NDC: 62991-1604 | Form: POWDER
Manufacturer: LETCO MEDICAL, LLC
Category: other | Type: BULK INGREDIENT - ANIMAL DRUG
Date: 20250627

ACTIVE INGREDIENTS: FLUNIXIN MEGLUMINE 1 g/1 g

Flunixin Meglumine

PACKAGE LABEL

Flunixin Meglumine USP 100g